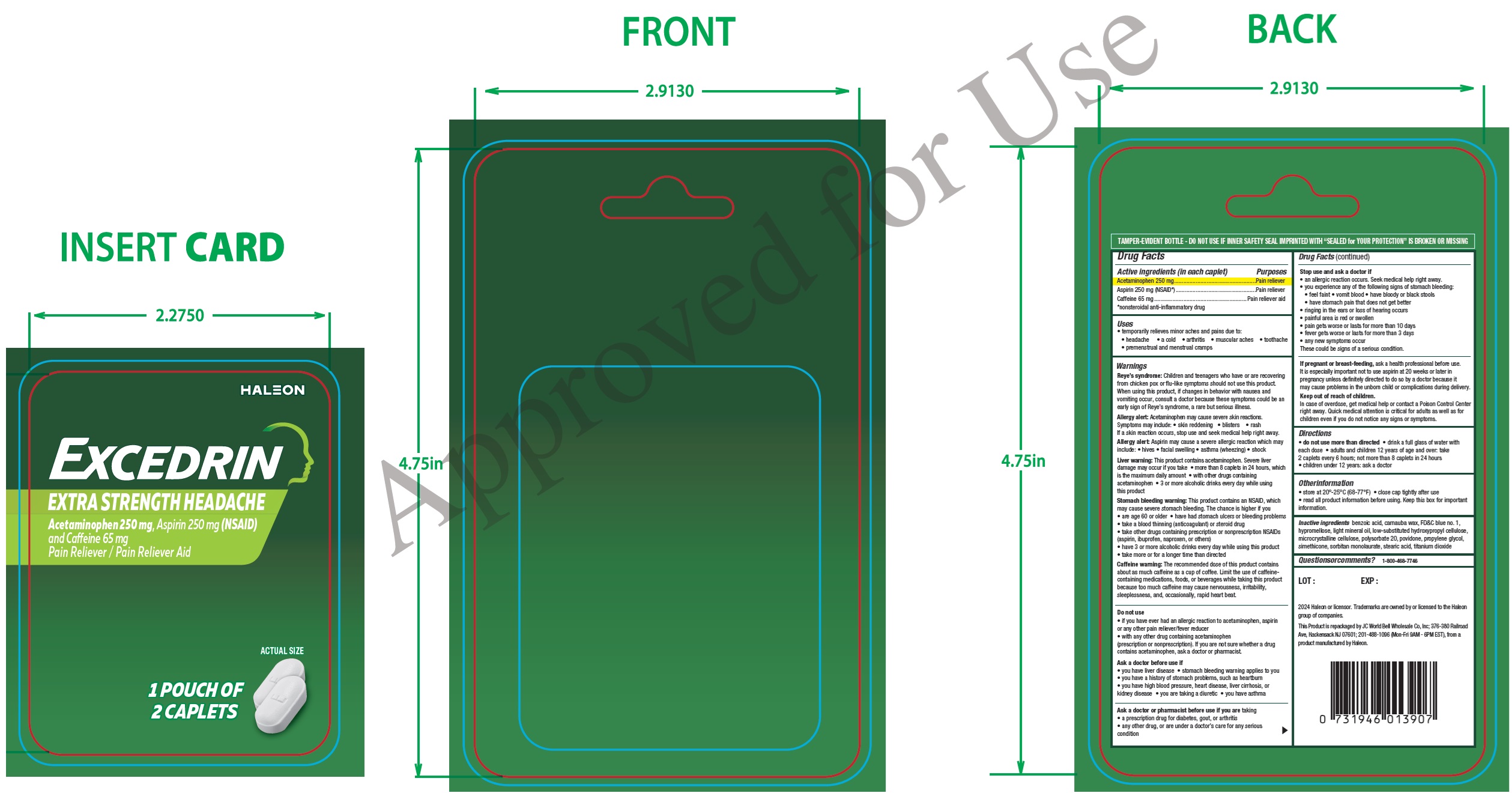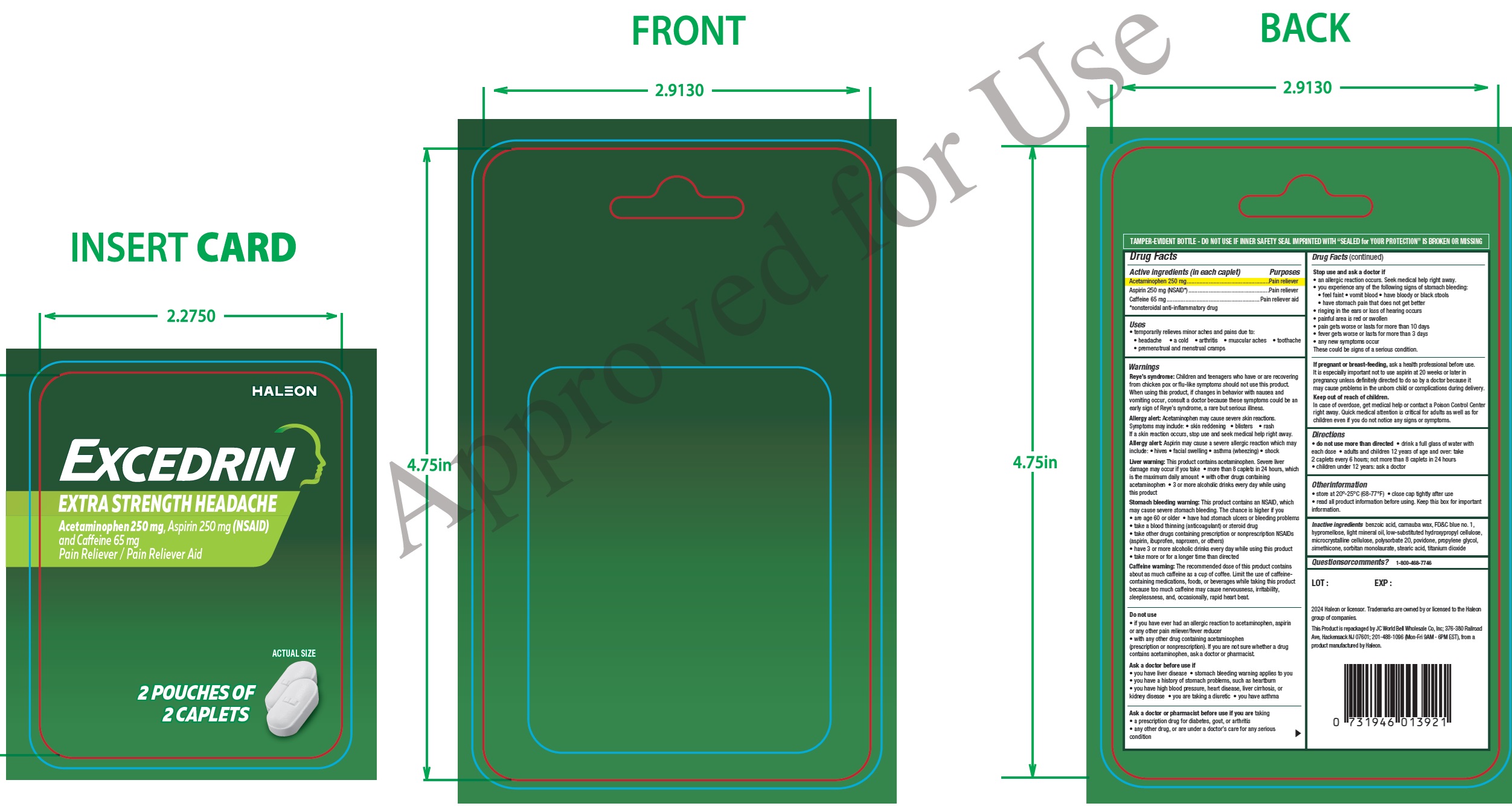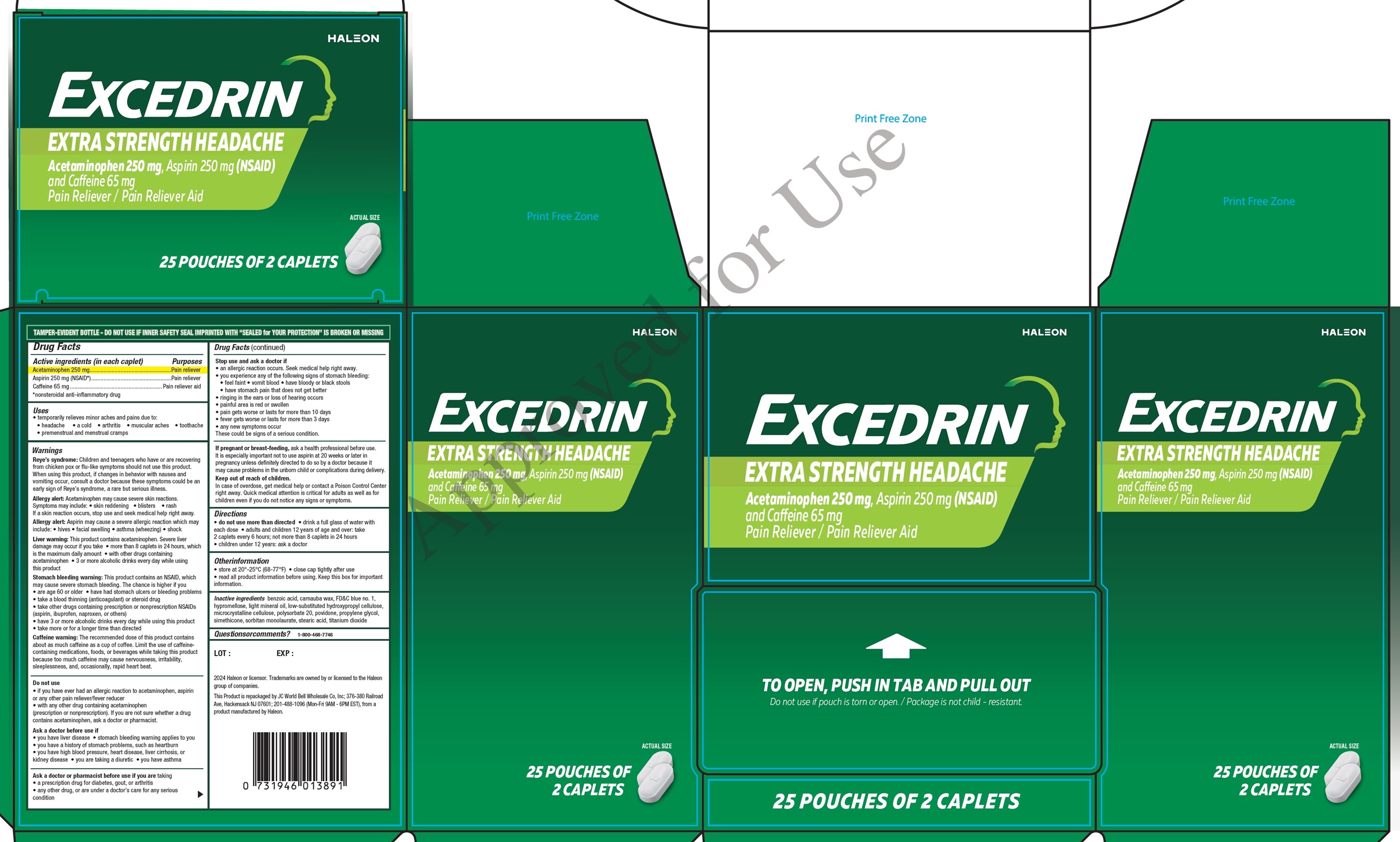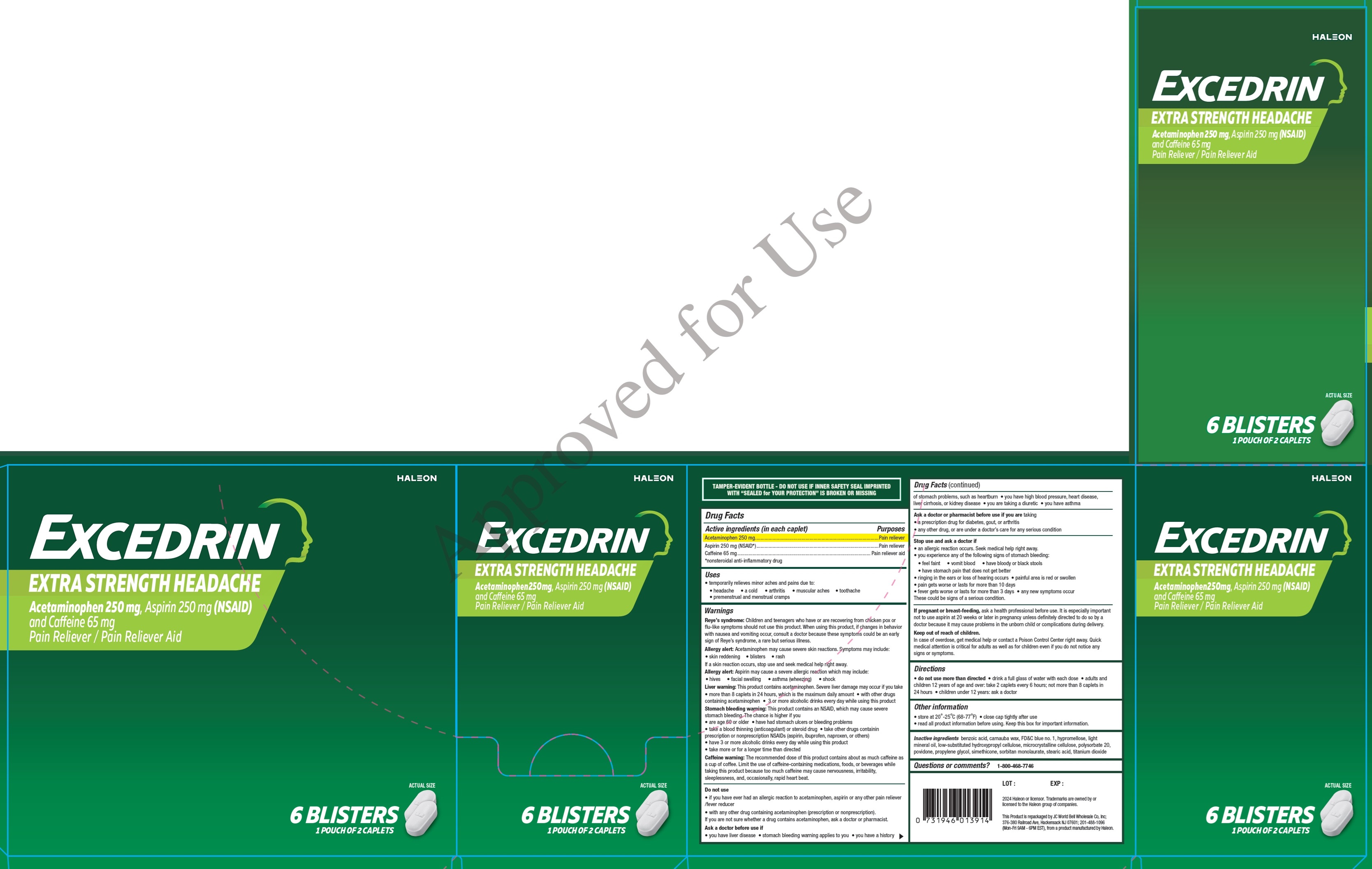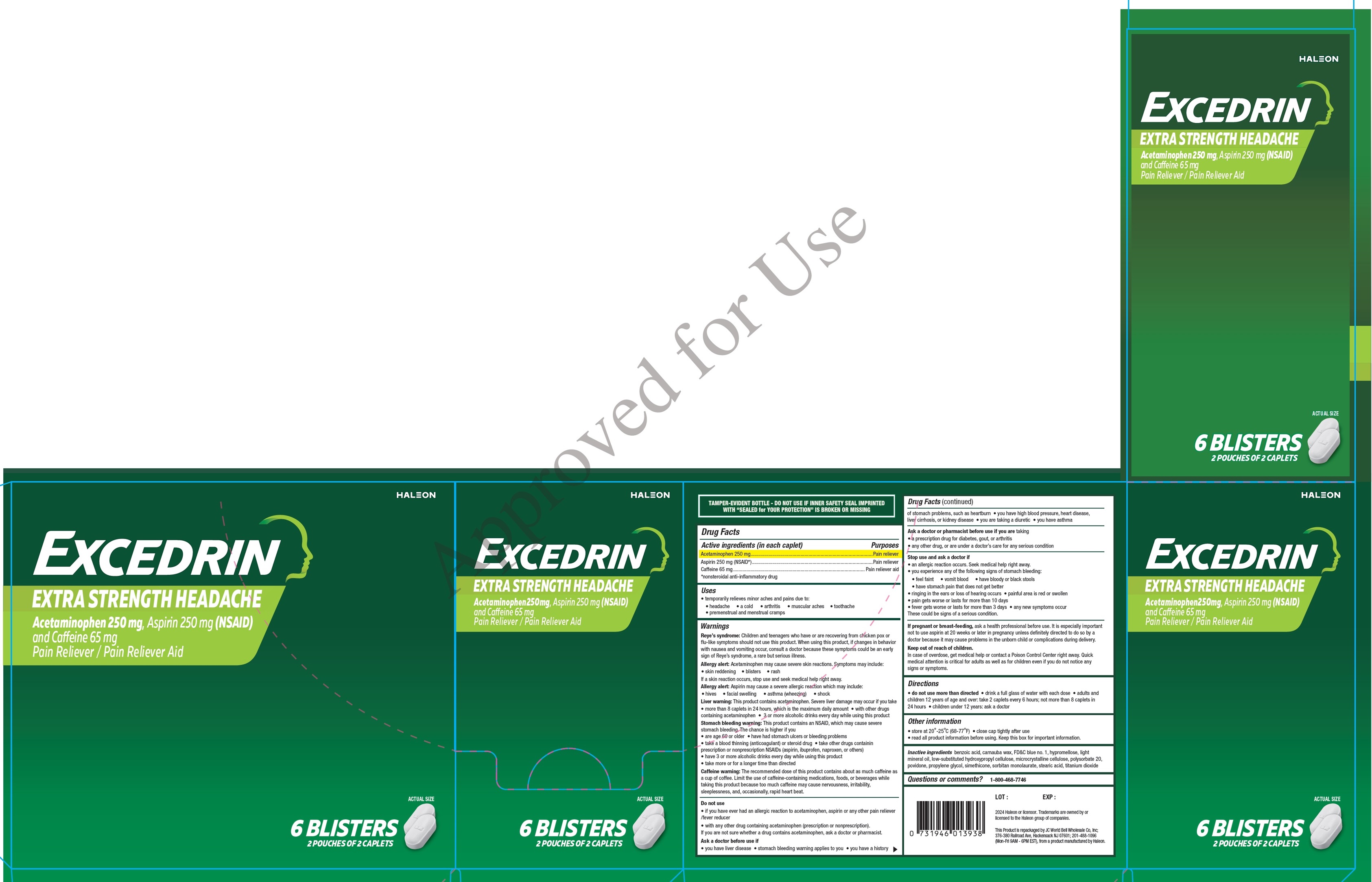 DRUG LABEL: Excedrin Extra Strength Headache
NDC: 50269-158 | Form: TABLET, FILM COATED
Manufacturer: JC World Bell Wholesale Co., Inc
Category: otc | Type: HUMAN OTC DRUG LABEL
Date: 20241223

ACTIVE INGREDIENTS: ACETAMINOPHEN 250 mg/1 1; ASPIRIN 250 mg/1 1; CAFFEINE 65 mg/1 1
INACTIVE INGREDIENTS: BENZOIC ACID; CARNAUBA WAX; FD&C BLUE NO. 1; HYPROMELLOSE, UNSPECIFIED; LIGHT MINERAL OIL; LOW-SUBSTITUTED HYDROXYPROPYL CELLULOSE, UNSPECIFIED; MICROCRYSTALLINE CELLULOSE; POLYSORBATE 20; POVIDONE; PROPYLENE GLYCOL; SORBITAN MONOLAURATE; STEARIC ACID; TITANIUM DIOXIDE

Excedrin Extra Strength Headache

Active ingredients (in each caplet)

Acetaminophen 250 mg

Aspirin 250 mg (NSAID*)

Caffeine 65 mg

Purposes

Pain reliever

Pain reliever

Pain reliever aid

*nonsteroidal anti-inflammatory drug

Uses

- temporarily relieves minor aches and pains due to:
- headache
- a cold
- arthritis
- muscular aches
- toothache
- premenstrual and menstrual cramps

Warnings

Reye’s syndrome:Children and teenagers who have or are recovering from chicken pox or flu-like symptoms should not use this product. When using this product, if changes in behavior with nausea and vomiting occur, consult a doctor because these symptoms could be an early sign of Reye’s syndrome, a rare but serious illness.

Allergy alert:Acetaminophen may cause severe skin reactions. Symptoms may include: • skin reddening • blisters • rash If a skin reaction occurs, stop use and seek medical help right away.

Allergy alert:Aspirin may cause a severe allergic reaction which may include: • hives • facial swelling • asthma (wheezing) • shock

Liver warning:This product contains acetaminophen. Severe liver damage may occur if you take • more than 8 caplets in 24 hours, which is the maximum daily amount • with other drugs containing acetaminophen • 3 or more alcoholic drinks every day while using this product

Stomach bleeding warning:This product contains an NSAID, which may cause severe stomach bleeding. The chance is higher if you
• are age 60 or older • have had stomach ulcers or bleeding problems • take a blood thinning (anticoagulant) or steroid drug • take other drugs containing prescription or nonprescription NSAIDs (aspirin, ibuprofen, naproxen, or others) • have 3 or more alcoholic drinks every day while using this product • take more or for a longer time than directed

Caffeine warning:The recommended dose of this product contains about as much caffeine as a cup of coffee. Limit the use of caffeinecontaining medications, foods, or beverages while taking this product because too much caffeine may cause nervousness, irritability, sleeplessness, and, occasionally, rapid heart beat.

Do not use

• if you have ever had an allergic reaction to acetaminophen, aspirin or any other pain reliever/fever reducer
• with any other drug containing acetaminophen (prescription or nonprescription). If you are not sure whether a drug contains acetaminophen, ask a doctor or pharmacist.

Ask a doctor before use if

• you have liver disease

• stomach bleeding warning applies to you

• you have a history of stomach problems, such as heartburn

• you have high blood pressure, heart disease, liver cirrhosis, or kidney disease

• you are taking a diuretic

• you have asthma

Ask a doctor or pharmacist before use if you are

taking
• a prescription drug for diabetes, gout, or arthritis
• any other drug, or are under a doctor’s care for any serious
condition

Stop use and ask a doctor if

• an allergic reaction occurs. Seek medical help right away.
• you experience any of the following signs of stomach bleeding:
• feel faint • vomit blood • have bloody or black stools
• have stomach pain that does not get better
• ringing in the ears or loss of hearing occurs
• painful area is red or swollen
• pain gets worse or lasts for more than 10 days
• fever gets worse or lasts for more than 3 days
• any new symptoms occur

These could be signs of a serious condition.

If pregnant or breast-feeding,

ask a health professional before use. It is especially important not to use aspirin at 20 weeks or later in pregnancy unless definitely directed to do so by a doctor because it may cause problems in the unborn child or complications during delivery.

Keep out of reach of children.

In case of overdose, get medical help or contact a Poison Control Center right away. Quick medical attention is critical for adults as well as for children even if you do not notice any signs or symptoms.

Directions

• do not use more than directed

• drink a full glass of water with each dose

• adults and children 12 years of age and over: take 2 caplets every 6 hours; not more than 8 caplets in 24 hours

• children under 12 years: ask a doctor

Otherinformation

• store at 20°-25°C (68-77°F)

• close cap tightly after use

• read all product information before using. Keep this box for important information.

Inactive ingredients

benzoic acid, carnauba wax, FD&C blue no. 1, hypromellose, light mineral oil, low-substituted hydroxypropyl cellulose, microcrystalline cellulose, polysorbate 20, povidone, propylene glycol, simethicone, sorbitan monolaurate, stearic acid, titanium dioxide

Questionsorcomments?

1-800-468-7746